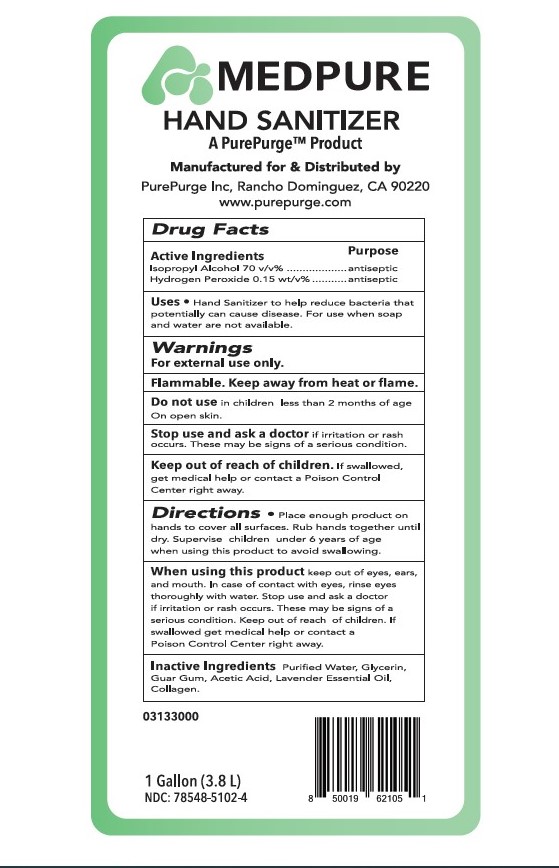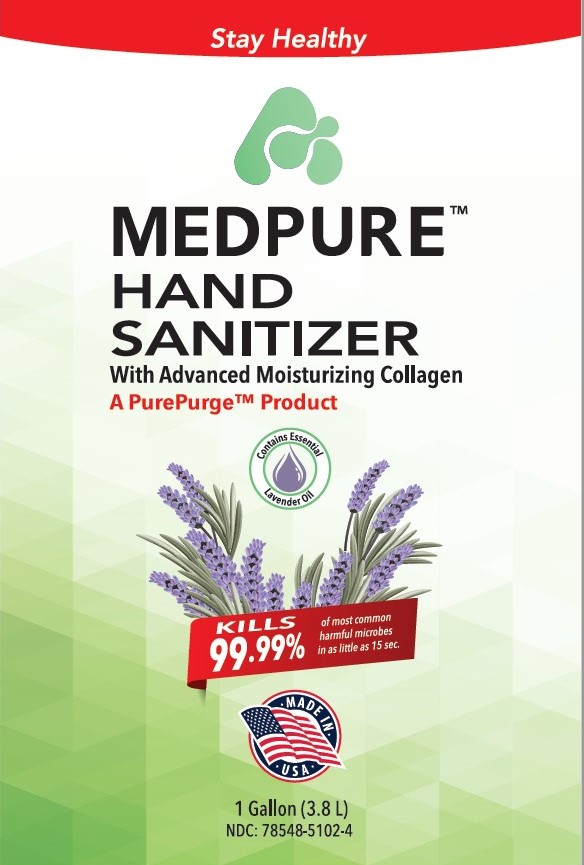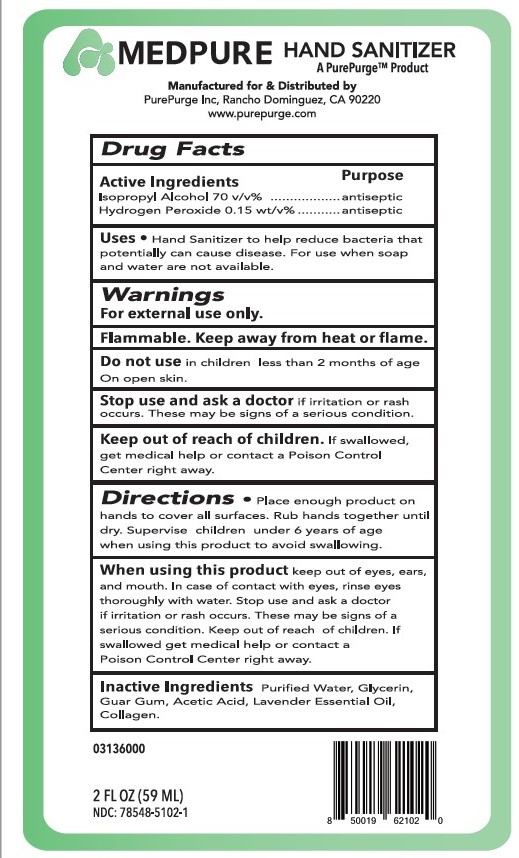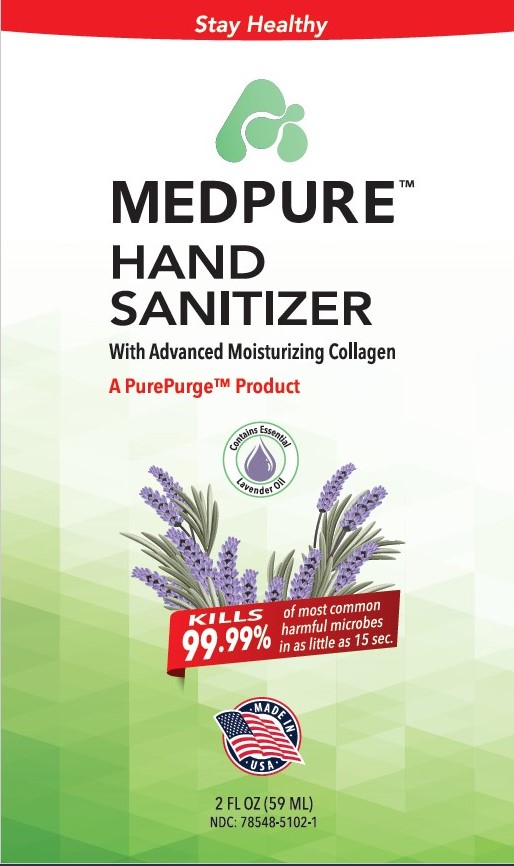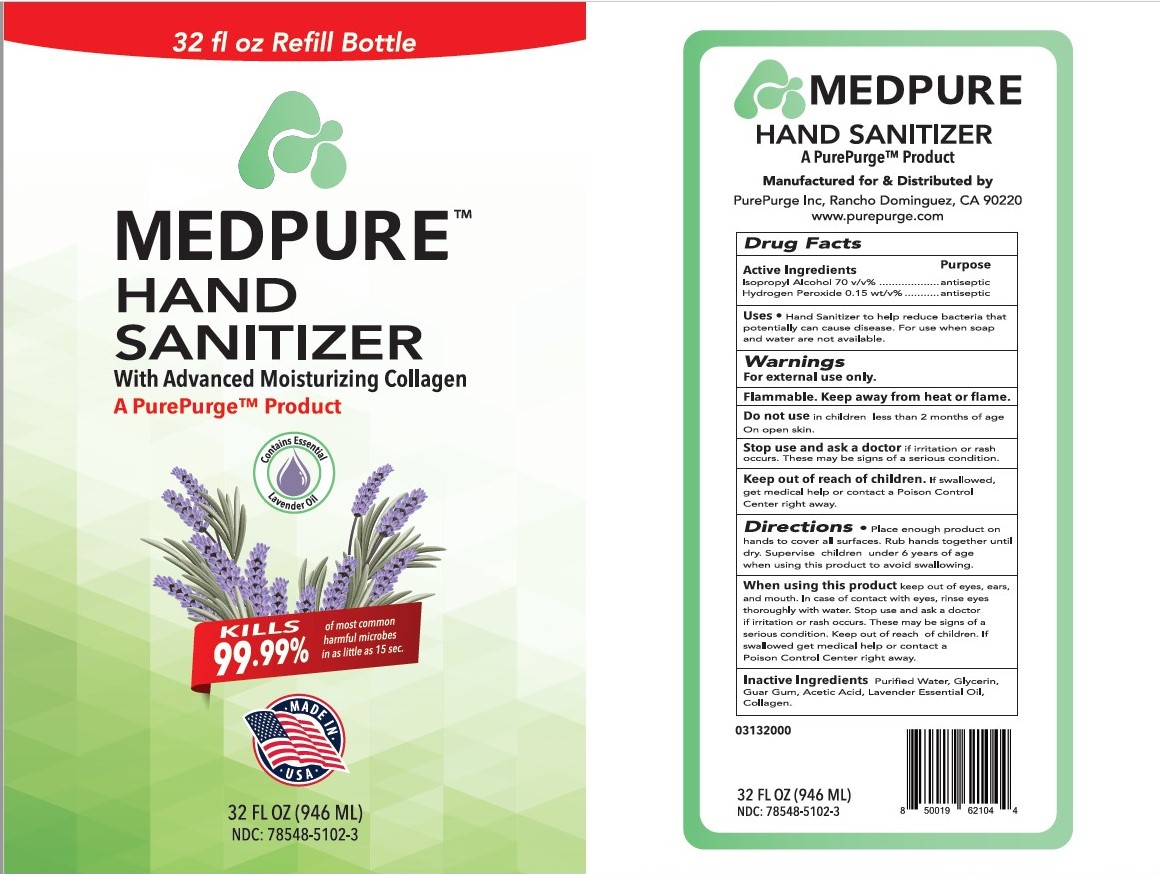 DRUG LABEL: Moisturizing Hand Sanitizer
NDC: 78548-5102 | Form: LIQUID
Manufacturer: Molecular GPS Enterprises dba Clayton Chemical
Category: otc | Type: HUMAN OTC DRUG LABEL
Date: 20220118

ACTIVE INGREDIENTS: ISOPROPYL ALCOHOL 700 mL/1000 mL
INACTIVE INGREDIENTS: GLYCERIN 20 mL/1000 mL; HYDROGEN PEROXIDE 4.2 mL/1000 mL; WATER 272.45 mL/1000 mL; LAVENDER OIL 2 mL/1000 mL; ACETIC ACID 0.1 mL/1000 mL; BOVINE TYPE I COLLAGEN 1 mL/1000 mL; GUAR GUM 0.25 mL/1000 mL

Moisturizing Hand Sanitizer

This is a hand sanitizer manufactured according to CFR Part333A and is manufactured using only the following United States Pharmacopoeia (USP) grade ingredients in the preparation of the product (percentage in final product formulation) consistent with World Health Organization (WHO) recommendations, ISO9001, and EN13485:

1. Isopropyl Alcohol (70%, v/v) in an aqueous solution denatured according to Alcohol and Tobacco Tax and Trade Bureau regulations in 27 CFR part 20.
2. Glycerol (2.0% v/v).
3. Lavender oil ((0.2% v/v).
4. Guar Gum (0.025% wt/v).
5. Glacial acetic acid (000% v/v)
6. Hydrogen peroxide (0.15% v/v).
7. Collagen (0.0003% wt/v).
8. Purified water.

The firm does not add other active or inactive ingredients. Different or additional ingredients may impact the quality and potency of the product.

Active Ingredient(s)

Isopropyl Alcohol 70% v/v. Purpose: Antiseptic

Purpose

Antiseptic, Hand Sanitizer

Use

Hand Sanitizer to help reduce bacteria that potentially can cause disease. For use when soap and water are not available.

Warnings

For external use only. Flammable. Keep away from heat or flame

Do not use

- in children less than 2 months of age
- on open skin wounds

When using this product keep out of eyes, ears, and mouth. In case of contact with eyes, rinse eyes thoroughly with water.
Stop use and ask a doctor if irritation or rash occurs. These may be signs of a serious condition.
Keep out of reach of children. If swallowed, get medical help or contact a Poison Control Center right away.

Stop use and ask a doctor if irritation or rash occurs. These may be signs of a serious condition.

Keep out of reach of children. If swallowed, get medical help or contact a Poison Control Center right away.

Directions

- Place enough product on hands to cover all surfaces. Rub hands together until dry.
- Supervise children under 6 years of age when using this product to avoid swallowing.

Other information

- Store between 15-30C (59-86F)
- Avoid freezing and excessive heat above 40C (104F)

Inactive ingredients

glycerin, lavender oil, guar gum, glacial acetic acid, hydrogen peroxide, collagen, purified water USP

Package Label - Principal Display Panel

59 ml NDC: 78548-5102-1

946 ml NDC: 78548-5102-3

3840 ml NDC: 78548-5102-4